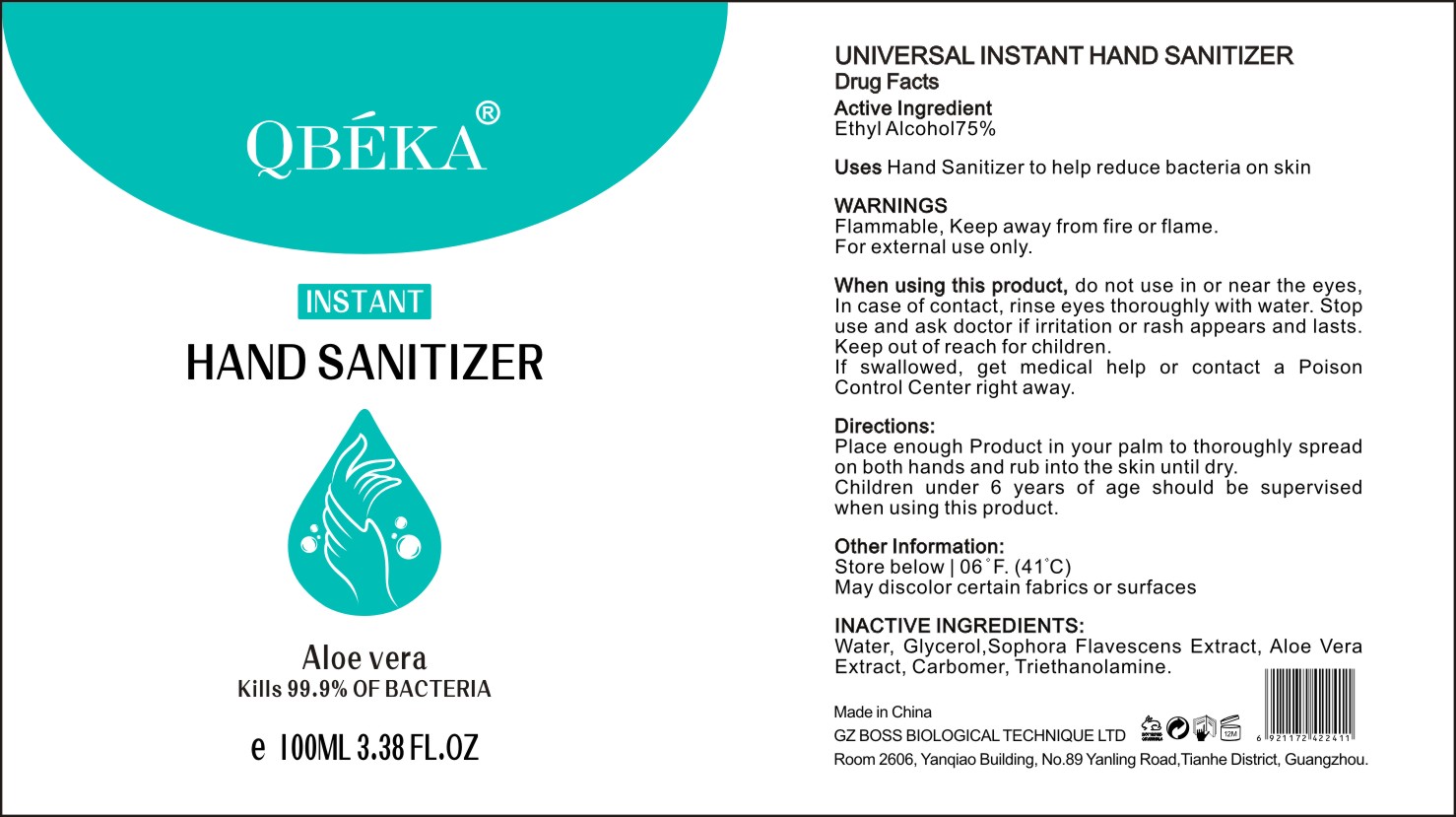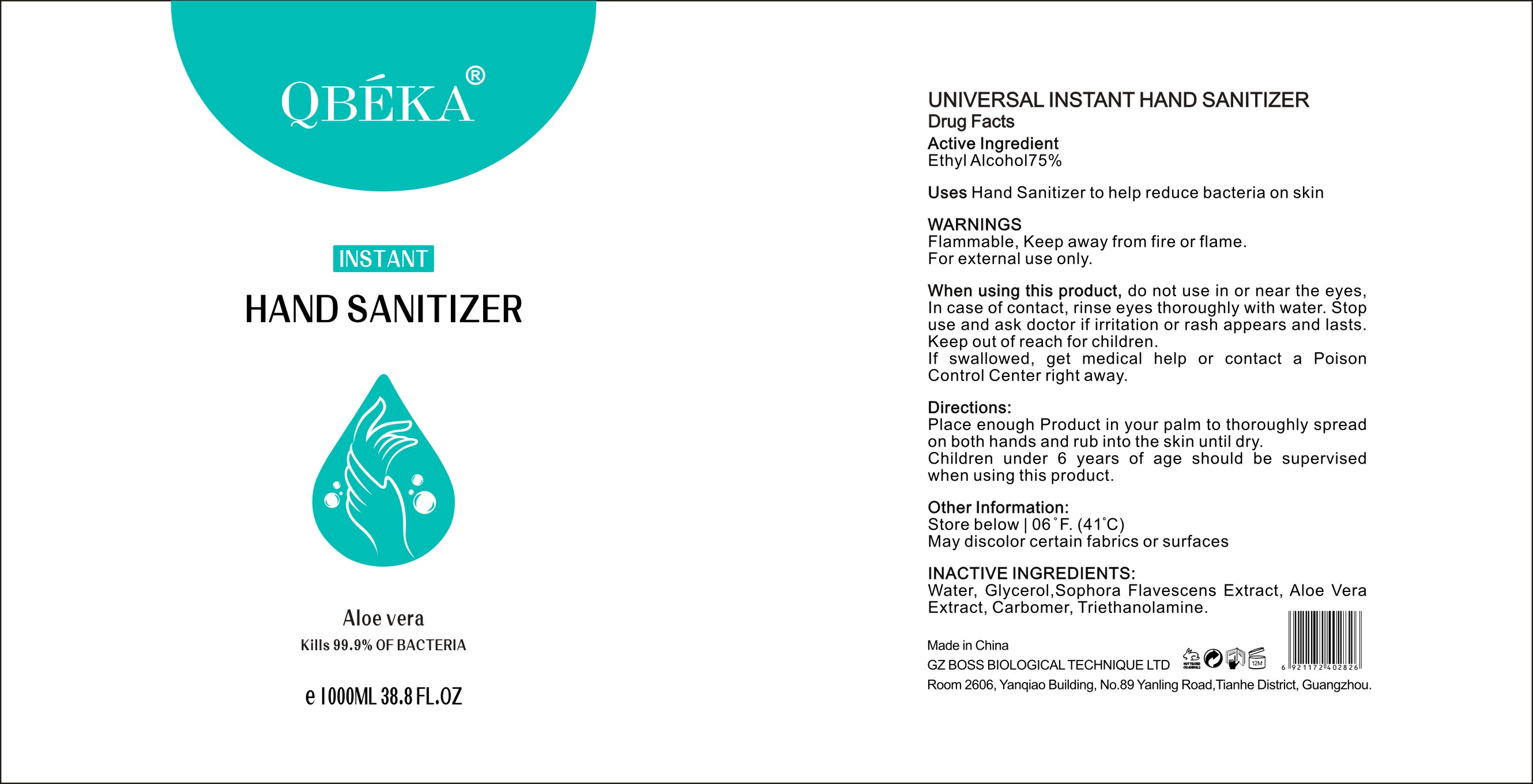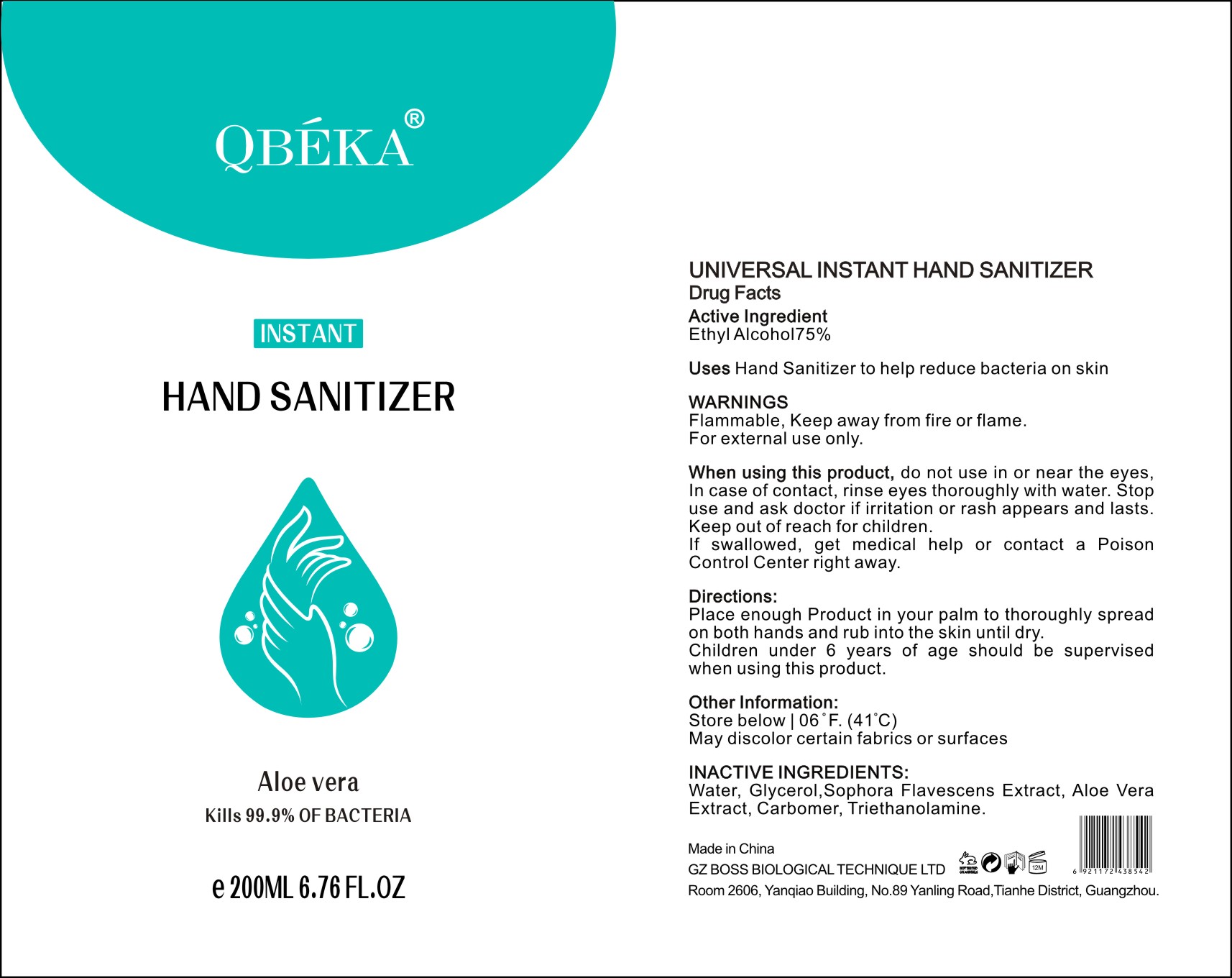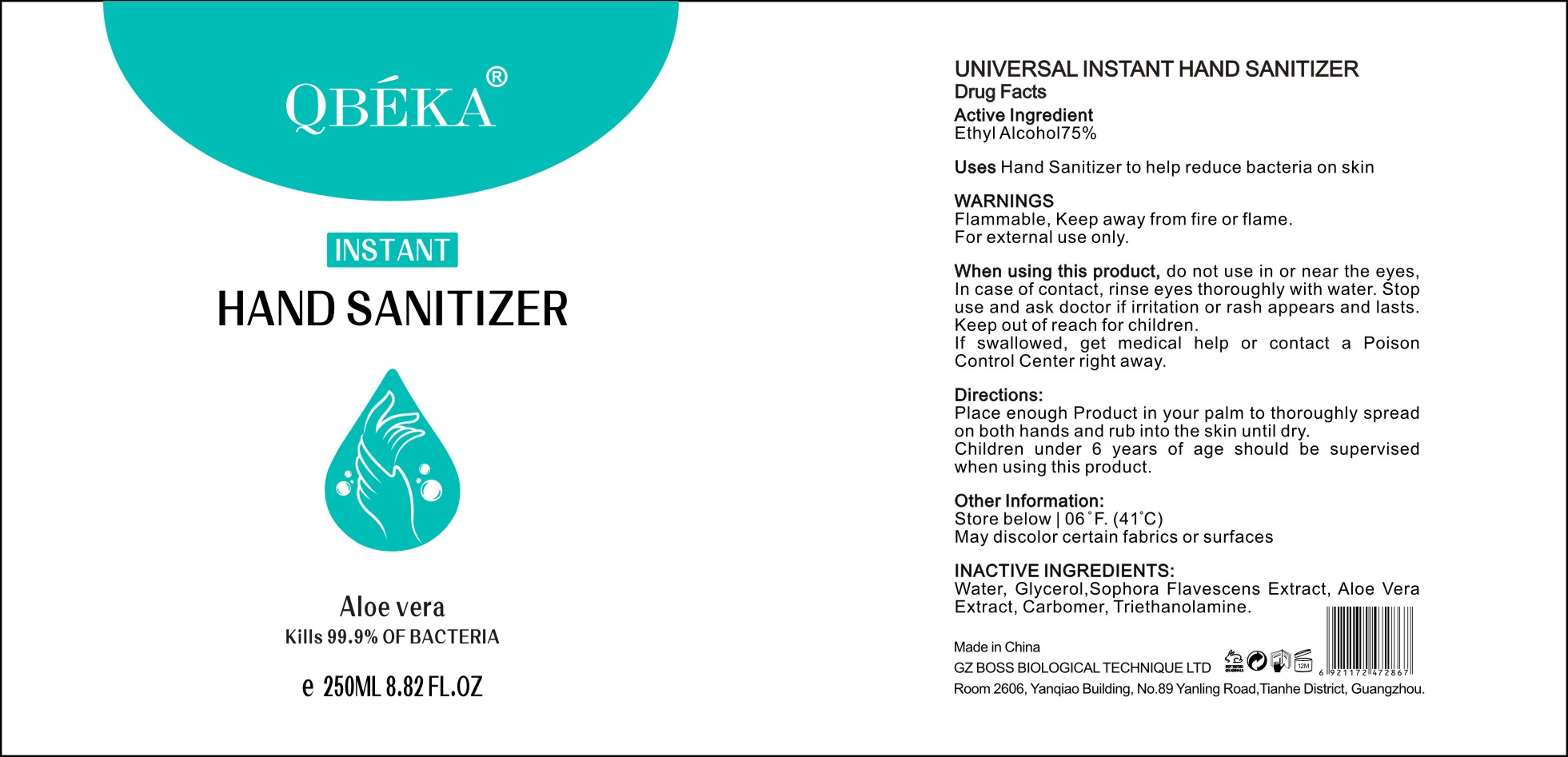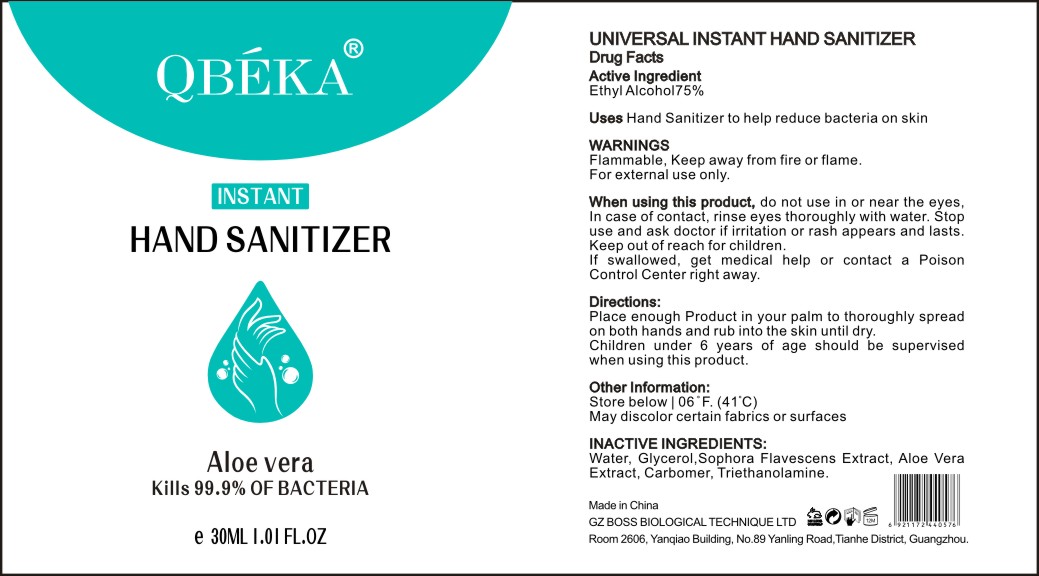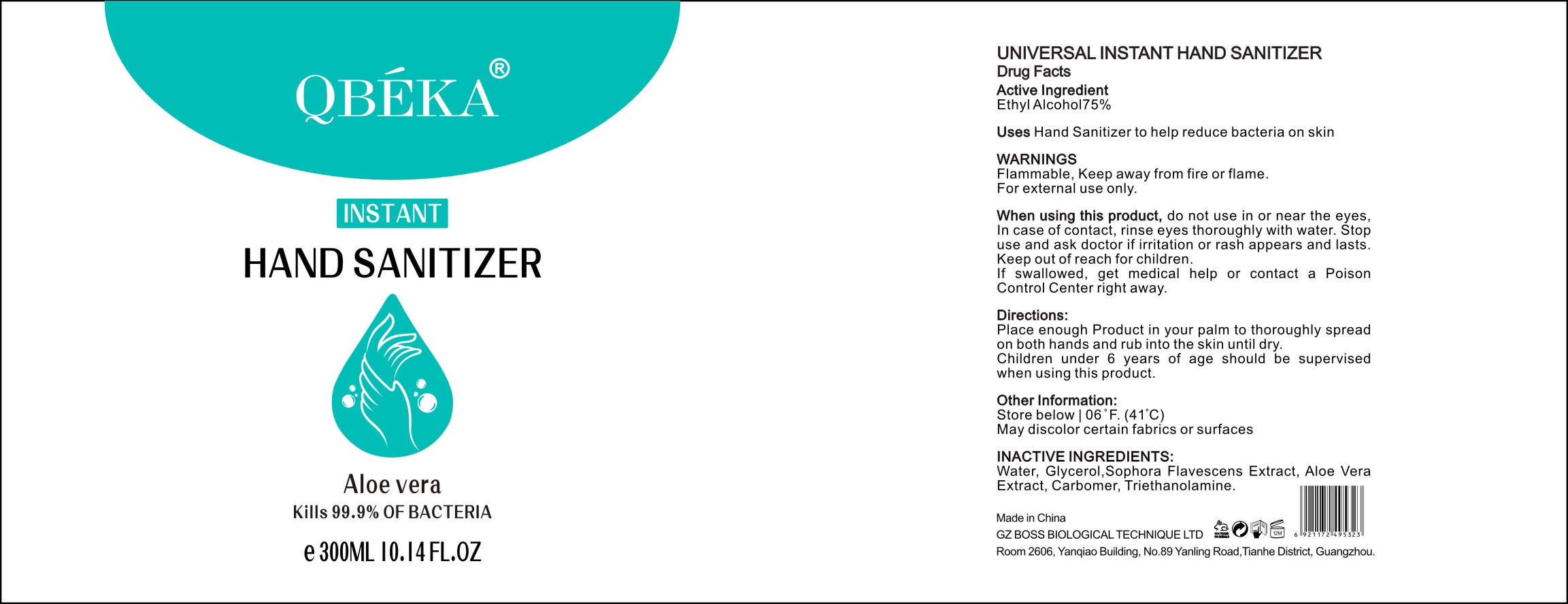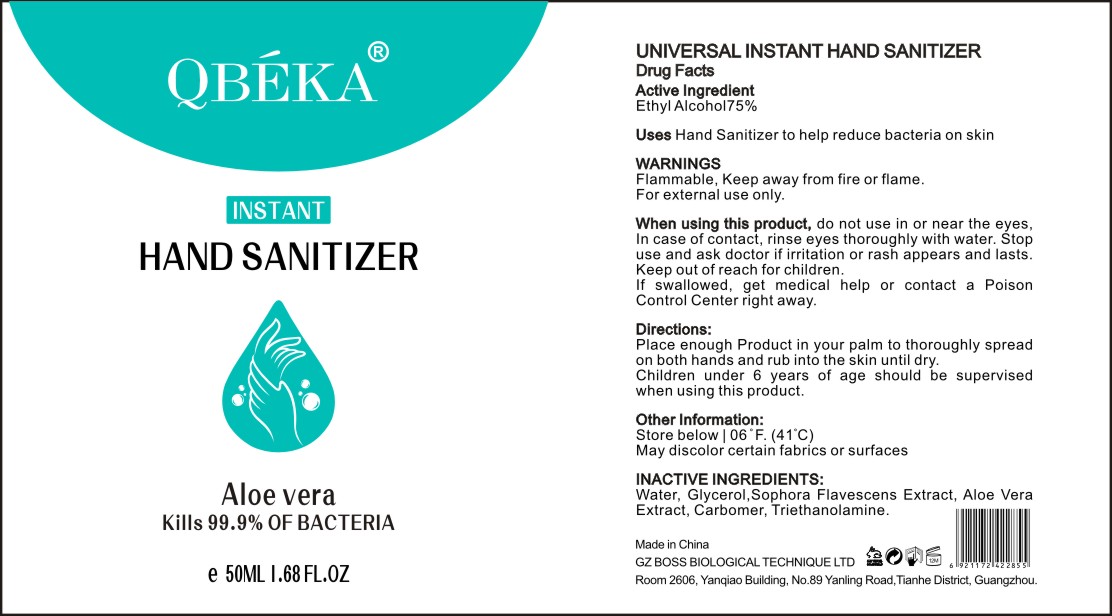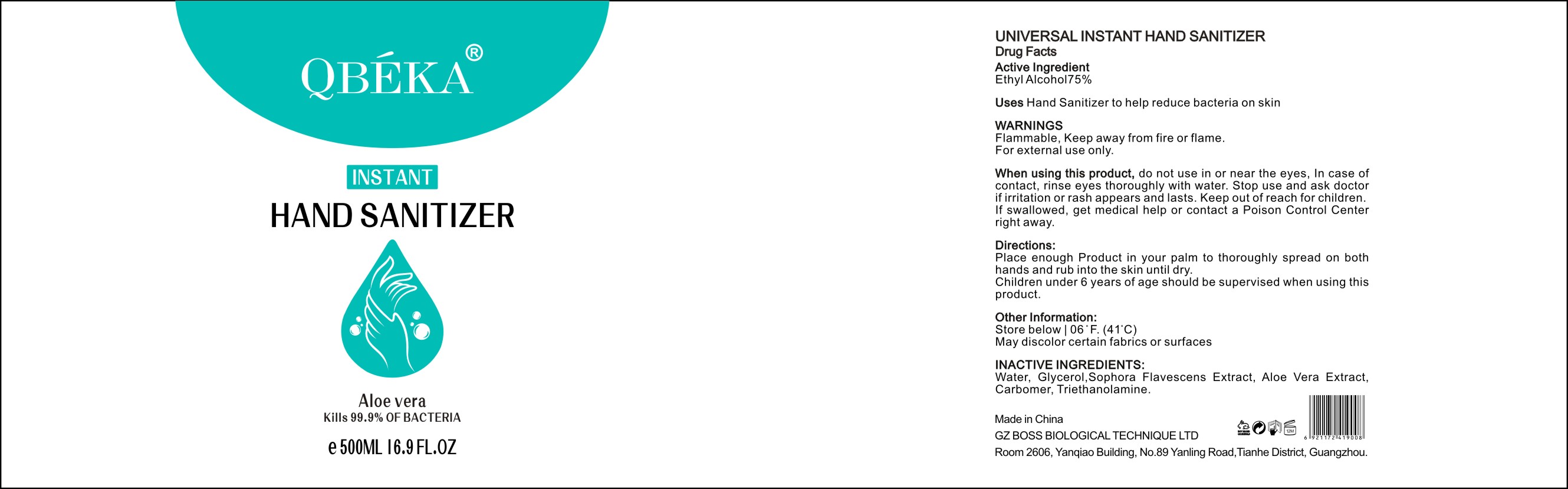 DRUG LABEL: Hand Sanitizer
NDC: 76762-006 | Form: LIQUID
Manufacturer: Guangzhou Boss Biological Technique Ltd.
Category: otc | Type: HUMAN OTC DRUG LABEL
Date: 20200514

ACTIVE INGREDIENTS: ALCOHOL 75 mL/100 mL
INACTIVE INGREDIENTS: TROLAMINE; GLYCERIN; WATER; SOPHORA FLAVESCENS ROOT; ALOE VERA LEAF; CARBOMER HOMOPOLYMER, UNSPECIFIED TYPE

Hand Sanitizer

Active Ingredient(s)

Ethyl Alcohol 75%

Purpose

Antimicrobial

Use

Hand sanitizer to help reduce bacteria on skin

Warnings

Flammable, Keep away from fire or flame.
For external use only.

do not use in or near the eyes.

When using this product, do not use in or near the eyes.
In case of contact, rinse eyes thoroughly with water. Stop use and ask doctor if irritation or rash appears and lasts.
Keep out of reach for children.
If swallowed, get medical help or contact a Poison Control Center right away.

Stop use and ask doctor if irritation or rash appears and lasts.

Keep out of reach for children.
If swallowed, get medical help or contact a Poison Control Center right away.

Directions

Place enough Product in your palm to thoroughly spread on both hands and rub into the skin until dry.
Children under 6 years of age should be supervised when using this product.

Other information

Store below 06 F(41°C).
May discolor certain fabrics or surfaces.

Inactive ingredients

Water, Glycerol, Sophora Flavescens Extract, Aloe VeraExtract, Carbomer, Triethanolamine